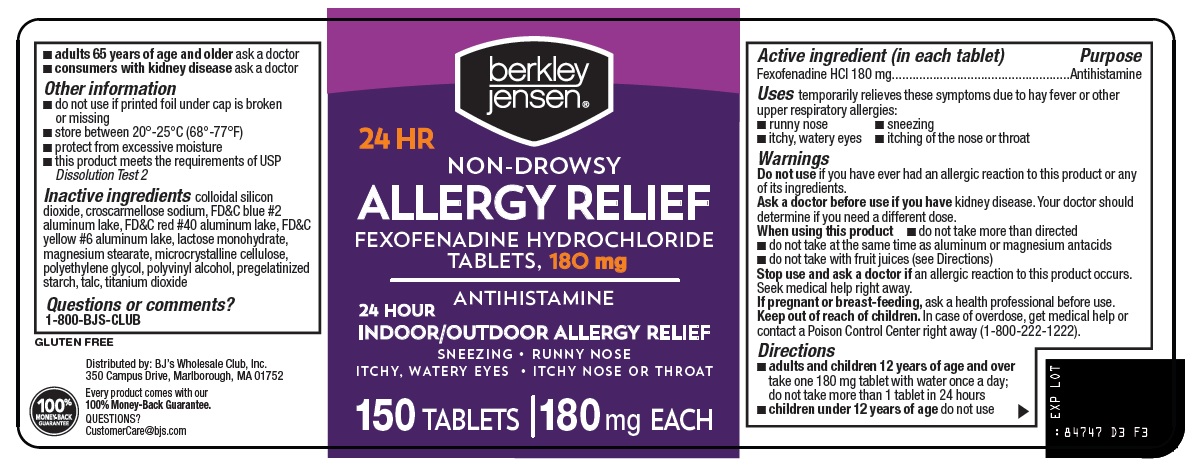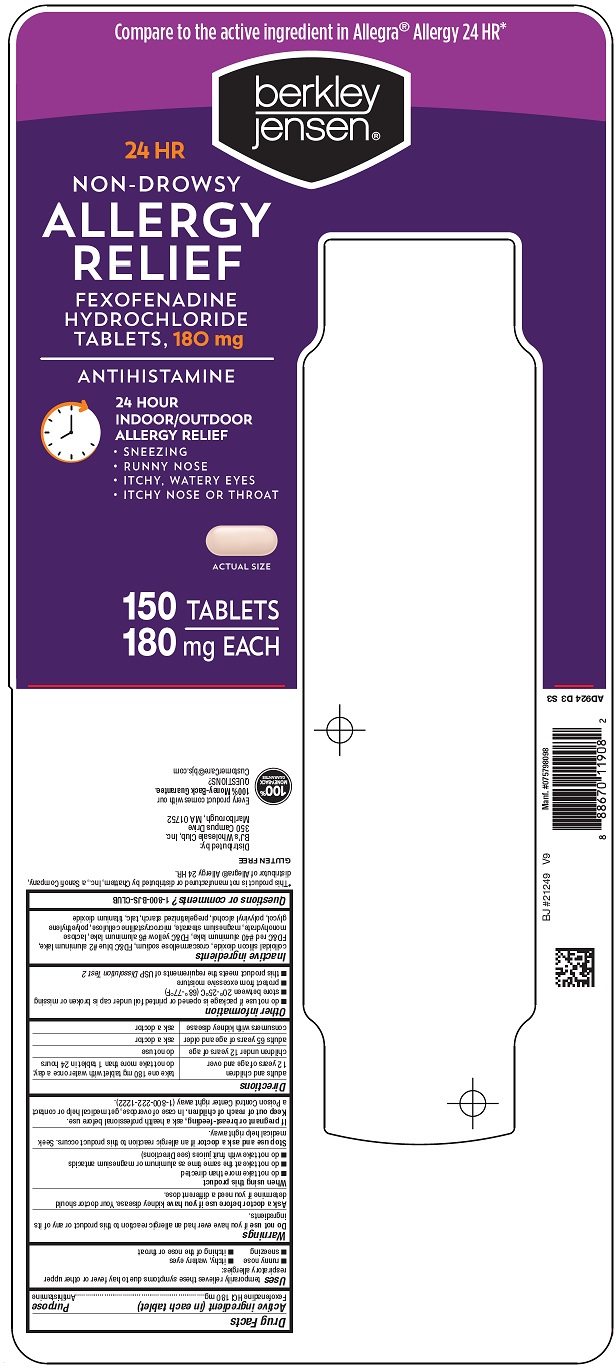 DRUG LABEL: berkley jensen allergy relief
NDC: 68391-847 | Form: TABLET, FILM COATED
Manufacturer: BJWC
Category: otc | Type: HUMAN OTC DRUG LABEL
Date: 20260206

ACTIVE INGREDIENTS: FEXOFENADINE HYDROCHLORIDE 180 mg/1 1
INACTIVE INGREDIENTS: SILICON DIOXIDE; CROSCARMELLOSE SODIUM; FD&C BLUE NO. 2 ALUMINUM LAKE; FD&C RED NO. 40 ALUMINUM LAKE; FD&C YELLOW NO. 6 ALUMINUM LAKE; LACTOSE MONOHYDRATE; MAGNESIUM STEARATE; MICROCRYSTALLINE CELLULOSE; POLYETHYLENE GLYCOL, UNSPECIFIED; POLYVINYL ALCOHOL, UNSPECIFIED; TALC; TITANIUM DIOXIDE

BJWC Allergy Relief Drug Facts

Active ingredient (in each tablet)

Fexofenadine HCl 180 mg

Purpose

Antihistamine

Uses

temporarily relieves these symptoms due to hay fever or other upper respiratory allergies:

- runny nose
- itchy, watery eyes
- sneezing
- itching of the nose or throat

Warnings

Do not use

if you have ever had an allergic reaction to this product or any of its ingredients.

Ask a doctor before use if you have

kidney disease. Your doctor should determine if you need a different dose.

When using this product

- do not take more than directed
- do not take at the same time as aluminum or magnesium antacids
- do not take with fruit juices (see Directions)

Stop use and ask a doctor if

an allergic reaction to this product occurs. Seek medical help right away.

If pregnant or breast-feeding,

ask a health professional before use.

Keep out of reach of children.

In case of overdose, get medical help or contact a Poison Control Center right away (1-800-222-1222).

Directions

adults and children 12 years of age and over | take one 180 mg tablet with water once a day; do not take more than 1 tablet in 24 hours
children under 12 years of age | do not use
adults 65 years of age and older | ask a doctor
consumers with kidney disease | ask a doctor

Other information

- do not use if package is opened or printed foil under cap is broken or missing
- store between 20°-25°C (68°-77°F)
- protect from excessive moisture
- this product meets the requirements of USP Dissolution Test 2

Inactive ingredients

colloidal silicon dioxide, croscarmellose sodium, FD&C blue #2 aluminum lake, FD&C red #40 aluminum lake, FD&C yellow #6 aluminum lake, lactose monohydrate, magnesium stearate, microcrystalline cellulose, polyethylene glycol, polyvinyl alcohol, pregelatinized starch, talc, titanium dioxide

Questions or comments?

1-800-BJS-CLUB

Principal Display Panel

Compare to the active ingredient in Allegra® Allergy 24 HR

berkley jensen®

24 HR

NON-DROWSY

ALLERGY RELIEF

FEXOFENADINE HYDROCHLORIDE TABLETS, 180 mg

ANTIHISTAMINE

24 HOUR INDOOR/OUTDOOR ALLERGY RELIEF

• SNEEZING

• RUNNY NOSE

• ITCHY, WATERY EYES

• ITCHY NOSE OR THROAT

ACTUAL SIZE

150 TABLETS

180 mg EACH

berkley jensen®

24 HR

NON-DROWSY

ALLERGY RELIEF

FEXOFENADINE HYDROCHLORIDE TABLETS, 180 mg

ANTIHISTAMINE

24 HOUR

INDOOR/OUTDOOR ALLERGY RELIEF

SNEEZING • RUNNY NOSE

ITCHY, WATERY EYES • ITCHY NOSE OR THROAT

150 TABLETS | 180 mg EACH